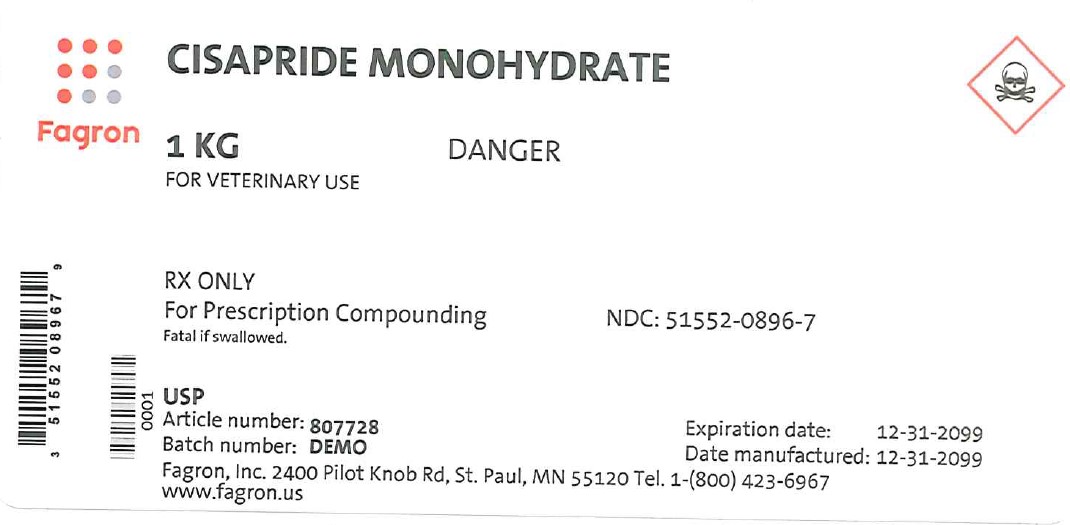 DRUG LABEL: Cisapride Monohydrate
NDC: 51552-0896 | Form: POWDER
Manufacturer: Fagron Inc
Category: other | Type: BULK INGREDIENT - ANIMAL DRUG
Date: 20231030

ACTIVE INGREDIENTS: CISAPRIDE MONOHYDRATE 1 g/1 g

Cisapride Monohydrate USP (Vet use only)